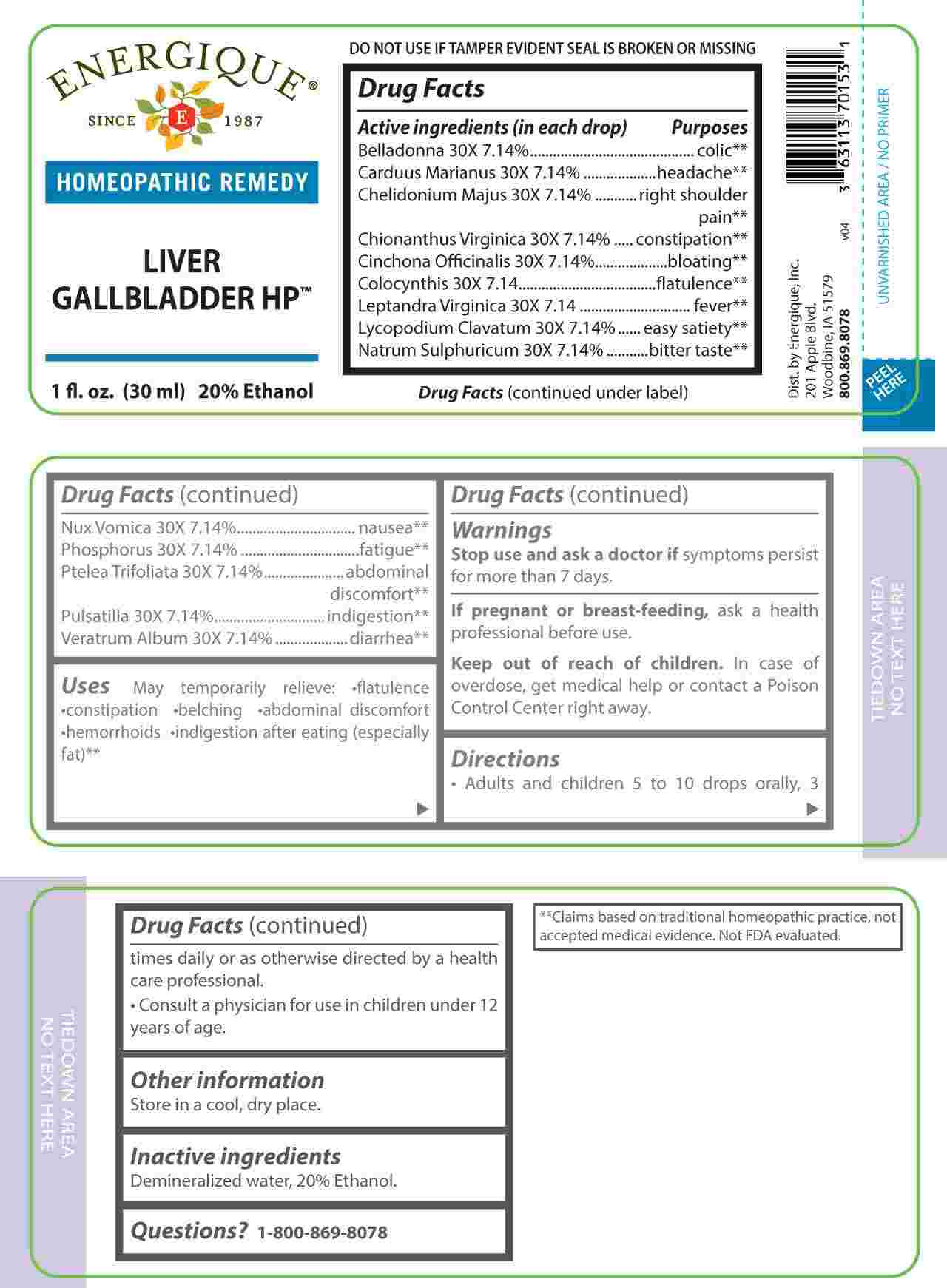 DRUG LABEL: Liver Gallbladder
NDC: 44911-0679 | Form: LIQUID
Manufacturer: Energique, Inc.
Category: homeopathic | Type: HUMAN OTC DRUG LABEL
Date: 20230804

ACTIVE INGREDIENTS: ATROPA BELLADONNA 30 [hp_X]/1 mL; MILK THISTLE 30 [hp_X]/1 mL; CHELIDONIUM MAJUS WHOLE 30 [hp_X]/1 mL; CHIONANTHUS VIRGINICUS ROOT BARK 30 [hp_X]/1 mL; CINCHONA OFFICINALIS BARK 30 [hp_X]/1 mL; CITRULLUS COLOCYNTHIS FRUIT PULP 30 [hp_X]/1 mL; VERONICASTRUM VIRGINICUM ROOT 30 [hp_X]/1 mL; LYCOPODIUM CLAVATUM SPORE 30 [hp_X]/1 mL; SODIUM SULFATE 30 [hp_X]/1 mL; STRYCHNOS NUX-VOMICA SEED 30 [hp_X]/1 mL; PHOSPHORUS 30 [hp_X]/1 mL; PTELEA TRIFOLIATA BARK 30 [hp_X]/1 mL; PULSATILLA PRATENSIS WHOLE 30 [hp_X]/1 mL; VERATRUM ALBUM ROOT 30 [hp_X]/1 mL
INACTIVE INGREDIENTS: WATER; ALCOHOL

DRUG FACTS:

ACTIVE INGREDIENTS:

(in each drop) Belladonna 30X 7.14%, Carduus Marianus 30X 7.14%, Chelidonium Majus 30X 7.14%, Chionanthus Virginica 30X 7.14%, Cinchona Officinalis 30X 7.14%, Colocynthis 30X 7.14%, Leptandra Virginica 30X 7.14%, Lycopodium Clavatum 30X 7.14%, Natrum Sulphuricum 30X 7.14%, Nux Vomica 30X 7.14%, Phosphorus 30X 7.14%, Ptelea Trifoliata 30X 7.14%, Pulsatilla 30X 7.14%, Veratrum Album 30X 7.14%.

PURPOSES:

Belladonna – colic,** Carduus Marianus - headache,** Chelidonium Majus – right shoulder pain,** Chionanthus Virginica - constipation, Cinchona Officinalis - bloating,** Colocynthis - flatulence,** Leptandra Virginica - fever,** Lycopodium Clavatum – easy satiety, Natrum Sulphuricum – bitter taste,** Nux Vomica - nausea,** Phosphorus - fatigue,** Ptelea Trifoliata – abdominal discomfort,** Pulsatilla - indigestion,** Veratrum Album - diarrhea.**

**Claims based on traditional homeopathic practice, not accepted medical evidence. Not FDA evaluated.

USES:

May temporarily relieve: •flatulence •constipation •belching •abdominal discomfort

•hemorrhoids •indigestion after eating (especially fat)**

**Claims based on traditional homeopathic practice, not accepted medical evidence. Not FDA evaluated.

WARNINGS:

Stop use and ask a doctor if symptoms persist for more than 7 days.

If pregnant or breast-feeding, ask a health professional before use.

Keep out of reach of children. In case of overdose, get medical help or contact a Poison Control Center right away.

DO NOT USE IF TAMPER EVIDENT SEAL IS BROKEN OR MISSING

Store in a cool, dry place.

KEEP OUT OF REACH OF CHILDREN:

In case of overdose, get medical help or contact a Poison Control Center right away.

DIRECTIONS:

• Adults and children 5 to 10 drops orally, 3 times daily or as otherwise directed by a health care professional.

• Consult a physician for use in children under 12 years of age.

INACTIVE INGREDIENTS:

Demineralized water, 20% Ethanol.

QUESTIONS:

Dist. by Energique, Inc.

201 Apple Blvd.

Woodbine, IA 51579

800.869.8078

PACKAGE LABEL DISPLAY:

ENERGIQUE

SINCE 1987

HOMEOPATHIC REMEDY

LIVER

GALLBLADDER HP

1 fl. oz. (30 ml)